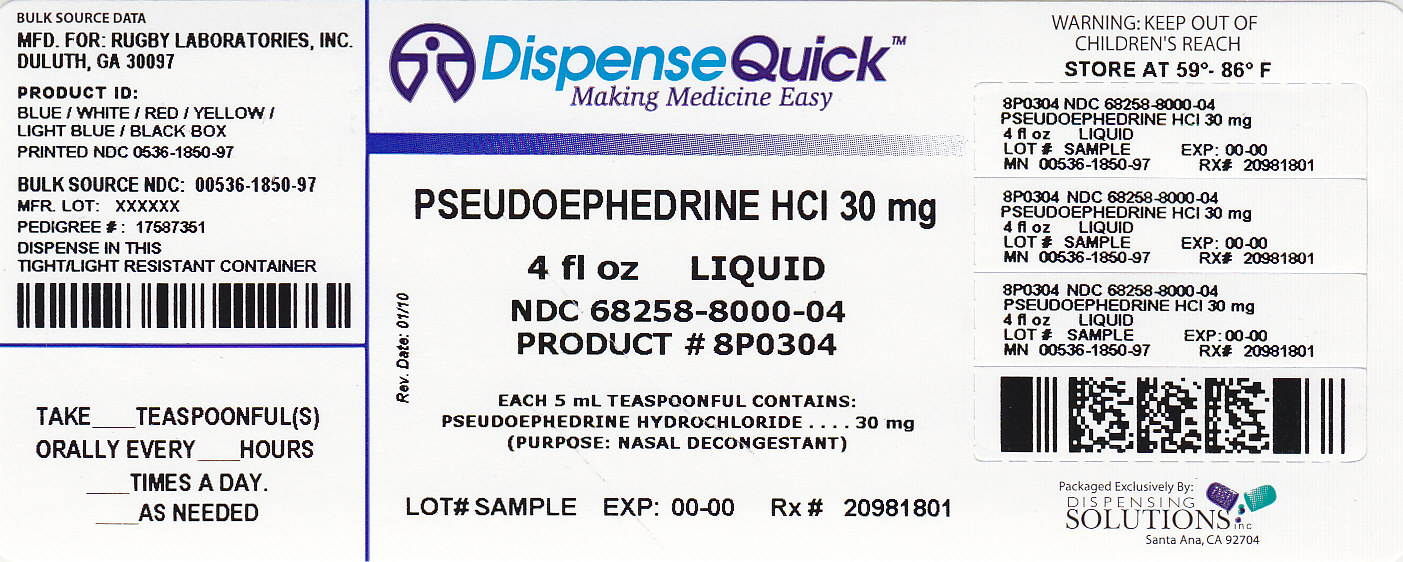 DRUG LABEL: Rugby Nasal Decongestant
NDC: 68258-8000 | Form: LIQUID
Manufacturer: Dispensing Solutions, Inc.
Category: otc | Type: HUMAN OTC DRUG LABEL
Date: 20111006

ACTIVE INGREDIENTS: Pseudoephedrine Hydrochloride 30 mg/5 mL
INACTIVE INGREDIENTS: Sorbitol; Citric Acid Monohydrate; Methylparaben; FD&C Red no. 40; Glycerin; Raspberry; Water; Sodium Benzoate; Saccharin Sodium

Rugby ®
NASAL
DECONGESTANT
LIQUID

Drug Facts

Active ingredient (in each teaspoonful [TSP])

Pseudoephedrine HCl 30 mg

Purpose

Nasal decongestant

Uses

temporarily relieves nasal congestion due to

- common cold
- hay fever
- upper respiratory allergies

Warnings

Do not use if you are now taking a prescription monoamine oxidase inhibitor (MAOI) (certain drugs for depression, psychiatric, or emotional conditions, or Parkinson's Disease), or for two weeks after stopping the MAOI drug. If you do not know if your prescription drug contains an MAOI, ask your doctor or pharmacist before taking this product.

Ask a doctor before use if you have

- heart disease
- thyroid disease
- diabetes
- high blood pressure
- trouble urinating due to an enlarged prostate gland

When using this product

- do not use more than directed

Stop use and ask a doctor if

- you get nervous, dizzy or sleepless
- symptoms do not improve within 7 days or occur with fever

PREGNANCY OR BREAST FEEDING

If pregnant or breast-feeding, ask a health professional before use.

Keep out of reach of children. In case of overdose, get medical help or contact a Poison Control Center right away.

Directions

- take every 4-6 hours
- do not take more than 4 doses in 24 hours
- use only with enclosed dose cup. Do not use with any other device.

adults & children 12 years and over | 2 TSP
children 6 to under 12 years | 1 TSP
children under 6 years | do not use

Other information

- store at room temperature 15°-30°C (59°-86°F)
- protect from light

Inactive ingredients

artificial raspberry flavor, citric acid, FD&C red #40, glycerin, methylparaben, purified water, saccharin sodium, sodium benzoate, sorbitol solution

Questions or comments?

Call 1-800-645-2158, 9 am - 5 pm ET, Monday - Friday

Mfd. for:
Rugby Laboratories, Inc.
Duluth, Georgia 30097

PRINCIPAL DISPLAY PANEL

NDC 68258-8000-04
NASAL DECONGESTANT
LIQUID
Pseudoephedrine HCl 30 mg
TEMPORARILY RELIEVES NASAL CONGESTION DUE TO COLDS AND ALLERGIES WITHOUT DROWSINESS
•SATISFACTION GUARANTEED•
4 fl oz
(118 mL)